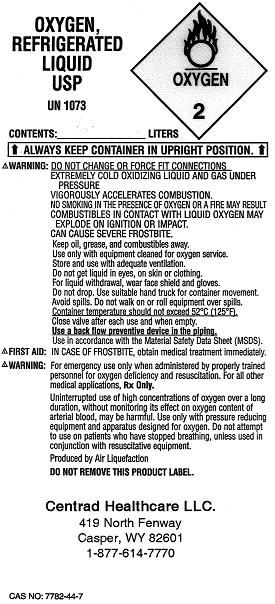 DRUG LABEL: Oxygen
NDC: 50093-001 | Form: GAS
Manufacturer: Centrad Healthcare, LLC
Category: prescription | Type: HUMAN PRESCRIPTION DRUG LABEL
Date: 20100209

ACTIVE INGREDIENTS: Oxygen 995 mL/1 L

Oxygen, Refrigerated Liquid USP